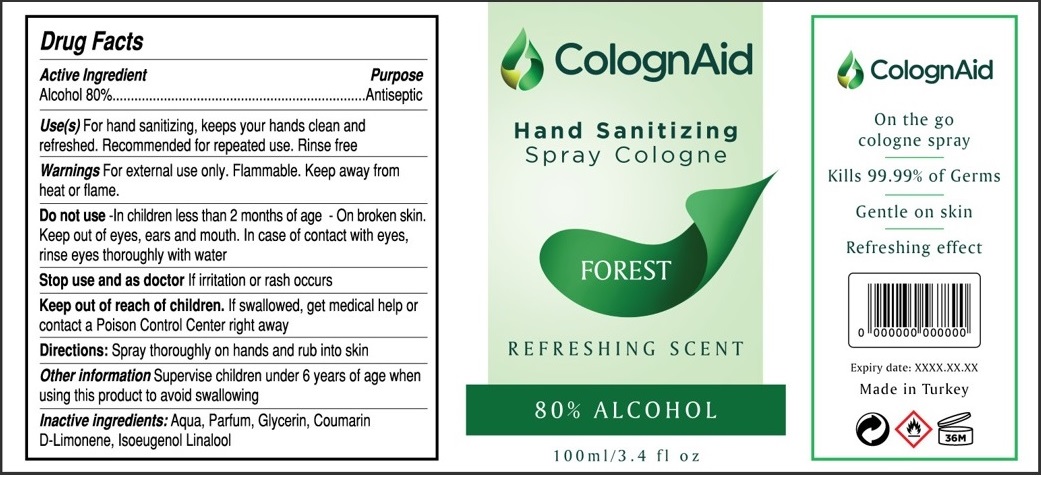 DRUG LABEL: ColognAid Hand Sanitizing FOREST
NDC: 81778-103 | Form: SPRAY
Manufacturer: NAREM KOZMETIK URUNLERI VE BILISIM SANAYI TICARET LIMITED SIRKETI
Category: otc | Type: HUMAN OTC DRUG LABEL
Date: 20210422

ACTIVE INGREDIENTS: ALCOHOL 80 mL/100 mL
INACTIVE INGREDIENTS: WATER; GLYCERIN; COUMARIN; LIMONENE, (+)-; ISOEUGENOL; LINALOOL, (+/-)-

ColognAid Hand Sanitizing Spray FOREST

Active Ingredient

Alcohol 80%

Purpose

Antiseptic

Use(s)

For hand sanitizing, keeps your hands clean and refreshed. Recommended for repeated use. Rinse free

Warnings

For external use only. Flammable. Keep away from heat or flame.

Do not use -In children less than 2 months of age - On broken skin. Keep out of eyes, ears and mouth. In case of contact with eyes, rinse eyes thoroughly with water

Stop use and ask doctor If irritation or rash occurs

Keep out of reach of children. If swallowed, get medical help or contact a Poison Control Center right away

Directions:

Spray thoroughly on hands and rub into skin

Other information

Supervise children under 6 years of age when using this product to avoid swallowing

Inactive ingredients:

Aqua, Parfum, Glycerin, Coumarin, D-Limonene, Isoeugenol, Linalool

Hand Sanitizing Spray Cologne

REFRESHING SCENT

On the go cologne spray

Kills 99.99% of Germs

Gentle on skin

Refreshing effect

Made in Turkey